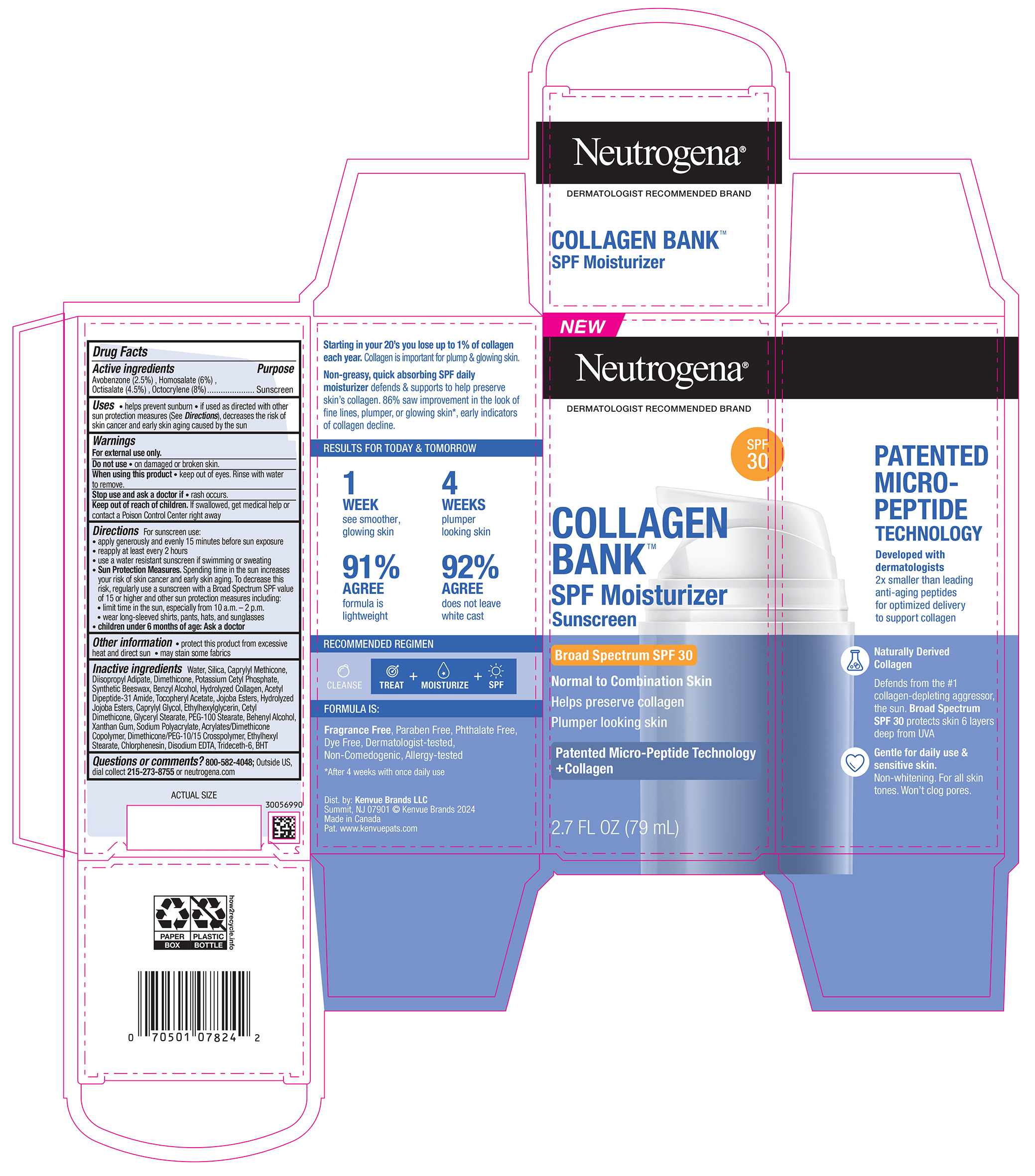 DRUG LABEL: Neutrogena Collagen Bank SPF Moisturizer Sunscreen Broad Spectrum SPF 30
NDC: 69968-0891 | Form: LOTION
Manufacturer: Kenvue Brands LLC
Category: otc | Type: HUMAN OTC DRUG LABEL
Date: 20250917

ACTIVE INGREDIENTS: OCTOCRYLENE 80 mg/1 mL; AVOBENZONE 25 mg/1 mL; OCTISALATE 45 mg/1 mL; HOMOSALATE 60 mg/1 mL
INACTIVE INGREDIENTS: CETYL DIMETHICONE 25; CAPRYLYL METHICONE; ALPHA-TOCOPHEROL ACETATE; PEG-100 STEARATE; DIISOPROPYL ADIPATE; SYNTHETIC BEESWAX; HYDROLYZED JOJOBA ESTERS (ACID FORM); XANTHAN GUM; 2-ETHYLHEXYL ACRYLATE, METHACRYLATE, METHYL METHACRYLATE, OR BUTYL METHACRYLATE/HYDROXYPROPYL DIMETHICONE COPOLYMER (30000-300000 MW); DIMETHICONE/PEG-10/15 CROSSPOLYMER; ETHYLHEXYL STEARATE; WATER; BHT; POTASSIUM CETYL PHOSPHATE; ETHYLHEXYLGLYCERIN; BEHENYL ALCOHOL; CHLORPHENESIN; EDETATE DISODIUM; BENZYL ALCOHOL; JOJOBA OIL, RANDOMIZED; GLYCERYL MONOSTEARATE; DIMETHICONE; SILICON DIOXIDE; CAPRYLYL GLYCOL; TRIDECETH-6

Neutrogena Collagen Bank SPF Moisturizer Sunscreen Broad Spectrum SPF 30

Drug Facts

Active ingredients

Avobenzone (2.5%), Homosalate (6%), Octisalate (4.5%), Octocrylene (8%)

Purpose

Sunscreen

Uses

- helps prevent sunburn
- if used as directed with other sun protection measures (see Directions), decreases the risk of skin cancer and early skin aging caused by the sun

Warnings

For external use only

Do not use • on damaged or broken skin

- When using this product • keep out of eyes. Rinse with water to remove.

Stop use and ask a doctor if • rash occurs

Keep out of reach of children. If swallowed, get medical help or contact a Poison Control Center right away

Directions

For sunscreen use:

- apply generously and evenly 15 minutes before sun exposure
- reapply at least every 2 hours
- use a water resistant sunscreen if swimming or sweating
- Sun Protection Measures. Spending time in the sun increases your risk of skin cancer and early skin aging. To decrease this risk, regularly use a sunscreen with a Broad Spectrum SPF value of 15 or higher and other sun protection measures including:
- limit time in the sun, especially from 10 a.m. – 2 p.m.
- wear long-sleeved shirts, pants, hats, and sunglasses
- children under 6 months of age: Ask a doctor

Other information

- protect this product from excessive heat and direct sun
- may stain some fabrics

Inactive ingredients

Water, Silica, Caprylyl Methicone, Diisopropyl Adipate, Dimethicone, Potassium Cetyl Phosphate, Synthetic Beeswax, Benzyl Alcohol, Hydrolyzed Collagen, Acetyl Dipeptide-31 Amide, Tocopheryl Acetate, Jojoba Esters, Hydrolyzed Jojoba Esters, Caprylyl Glycol, Ethylhexylglycerin, Cetyl Dimethicone, Glyceryl Stearate, PEG-100 Stearate, Behenyl Alcohol, Xanthan Gum, Sodium Polyacrylate, Acrylates/Dimethicone Copolymer, Dimethicone/PEG-10/15 Crosspolymer, Ethylhexyl Stearate, Chlorphenesin, Disodium EDTA, Trideceth-6, BHT

Questions or comments?

800-582-4048; Outside US, dial collect 215-273-8755 or neutrogena.com.

Distributed by:
Kenvue Brands LLC

Summit, NJ 07901

PRINCIPAL DISPLAY PANEL - 79 mL Bottle Carton

NEW

Neutrogena®

DERMATOLOGIST RECOMMENDED BRAND

SPF

30

COLLAGEN

BANK™

SPF Moisturizer

Sunscreen

Broad Spectrum SPF 30

Normal to Combination Skin

Helps preserve collagen

Plumper looking skin

Patented Micro-Peptide Technology

+Collagen

2.7 FL OZ (79 mL)